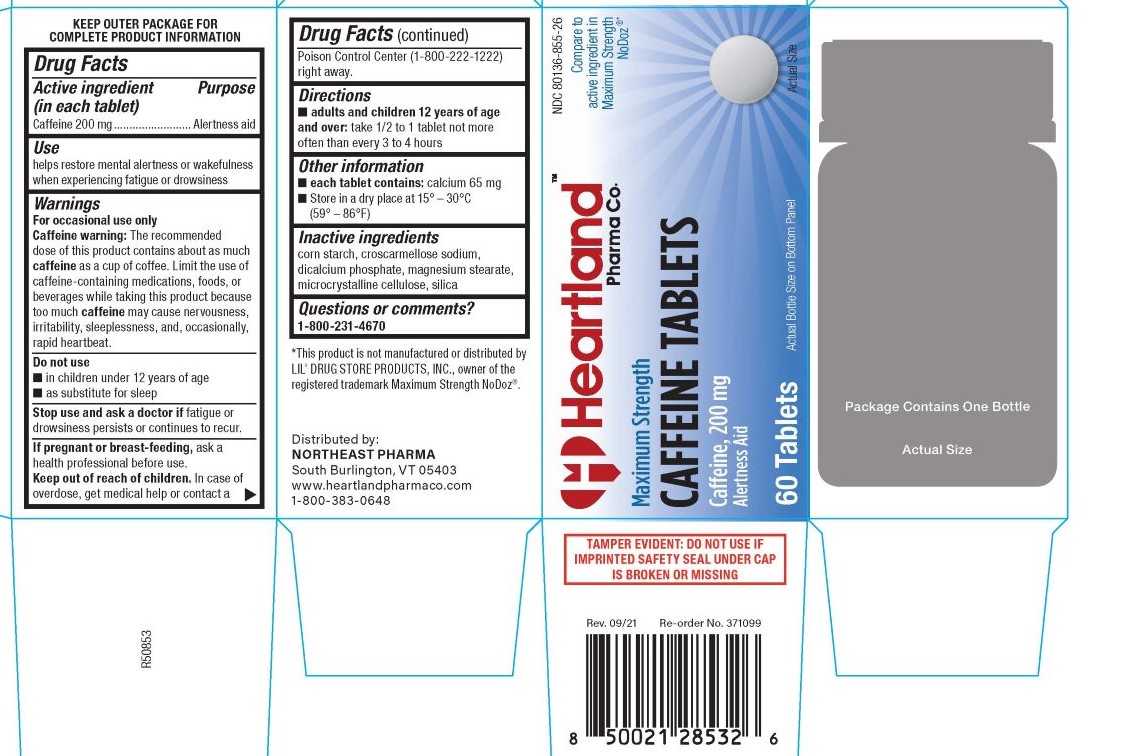 DRUG LABEL: Caffeine
NDC: 80136-855 | Form: TABLET
Manufacturer: Northeast Pharma
Category: otc | Type: HUMAN OTC DRUG LABEL
Date: 20220915

ACTIVE INGREDIENTS: CAFFEINE 200 mg/1 1
INACTIVE INGREDIENTS: DIBASIC CALCIUM PHOSPHATE DIHYDRATE; CROSCARMELLOSE SODIUM; MICROCRYSTALLINE CELLULOSE; STARCH, CORN; SILICON DIOXIDE; MAGNESIUM STEARATE

5350-Hartland

Drug Facts

Active ingredient (in each tablet)
Caffeine 200 mg

Purpose
Alertness aid

Use

helps restore mental alertness or wakefulness when experiencing fatigue or drowsiness

WARNINGS

For occasional use only
Caffeine warning: The recommended dose of this product contains about as much caffeine as a cup of coffee. Limit the use of
caffeine-containing medications, foods, or beverages while taking this product because too much caffeine may cause nervousness,
irritability, sleeplessness, and, occasionally, rapid heartbeat.

Do not use
■ in children under 12 years of age
■ as substitute for sleep

Stop use and ask a doctor if fatigue or drowsiness persists or continues to recur.

PREGNANCY OR BREAST FEEDING

If pregnant or breast-feeding, ask a health professional before use.

Keep out of reach of children.

OVERDOSAGE

In case of overdose, get medical help or contact a Poison Control Center (1-800-222-1222) right away.

Directions

■ adults and children 12 years of age and over: take 1/2 to 1 tablet not more often than every 3 to 4 hours

Other information

■ each tablet contains: calcium 65 mg
■ Store in a dry place at 15° – 30°C (59° – 86°F)

INACTIVE INGREDIENT

corn starch, croscarmellose sodium, dicalcium phosphate, magnesium stearate, microcrystalline cellulose, silica

Questions or comments?

1-800-231-4670

KEEP OUTER PACKAGE FOR COMPLETE PRODUCT INFORMATION

Distributed by:
NORTHEAST PHARMA
South Burlington, VT 05403
www.heartlandpharmaco.com
1-800-383-0648

TAMPER EVIDENT: DO NOT USE IF IMPRINTED SAFETY SEAL UNDER CAP IS BROKEN OR MISSING

*This product is not manufactured or distributed by LIL' DRUG STORE PRODUCTS, INC., owner of the registered trademark Maximum Strength NoDoz®.

PACKAGE LABEL

NDC 80136-855-26

Compare to active ingredient in Maximum Strength NoDoz ®*

Heartland Pharma Co.

Maximum Strength

Caffeine Tablets

Caffeine, 200 mg

Alertness Aid

60 Tablets